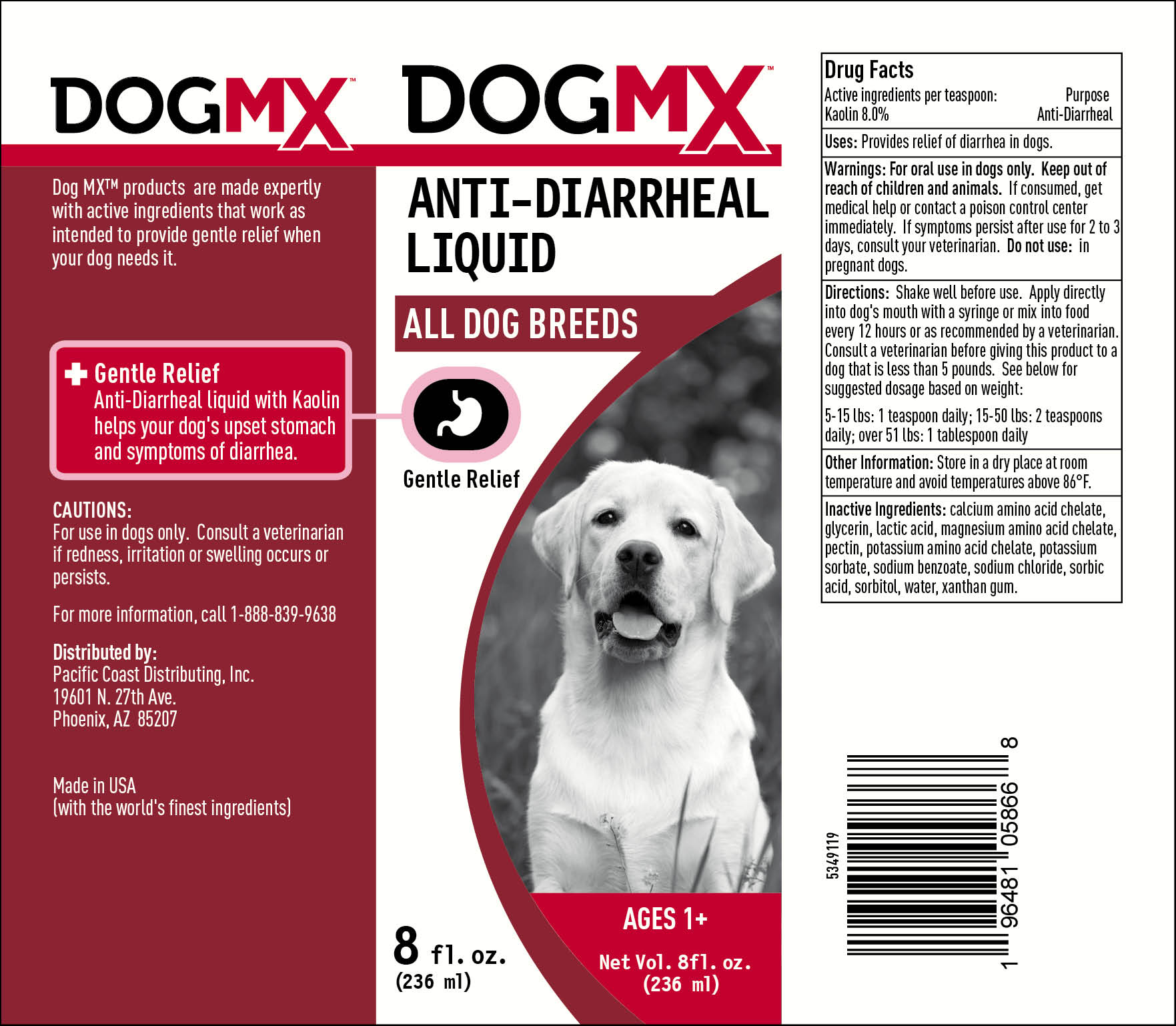 DRUG LABEL: DOG MX ANTI-DIARRHEAL
NDC: 86195-866 | Form: SOLUTION
Manufacturer: TRIDENT SEAFOODS
Category: animal | Type: OTC ANIMAL DRUG LABEL
Date: 20240125

ACTIVE INGREDIENTS: KAOLIN 8 g/100 mL
INACTIVE INGREDIENTS: Pectin; WATER; GLYCERIN; SORBIC ACID; XANTHAN GUM; SORBITOL; SODIUM BENZOATE; POTASSIUM SORBATE; CALCIUM; MAGNESIUM; SODIUM CHLORIDE; LACTIC ACID

DOG MX ANTI-DIARRHEAL 8OZ

ACTIVE INGREDIENTS PER TEASPOON

KAOLIN 8.0%

PURPOSE

DIARRHEA RELIEF

WARNINGS

For oral use in dogs only. Keep out of reach of children and animals. If consumed, get medical hep or contact poison control center immediately. If symptoms persist after use for 2 to 3 days, consult your veterinarian. DO NOT USE: In pregnant dogs.